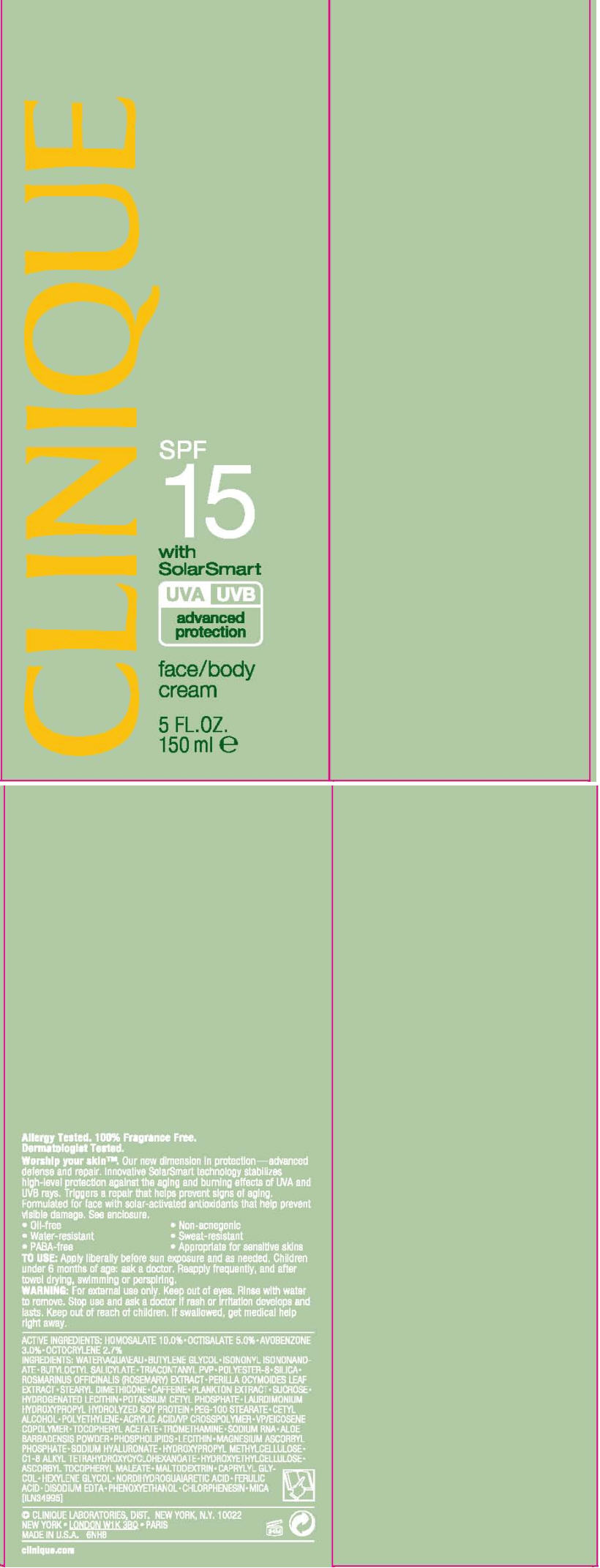 DRUG LABEL: CLINIQUE 
NDC: 49527-735 | Form: CREAM
Manufacturer: CLINIQUE  LABORATORIES INC.
Category: otc | Type: HUMAN OTC DRUG LABEL
Date: 20120806

ACTIVE INGREDIENTS: homosalate 10 mL/100 mL; octisalate 5 mL/100 mL; avobenzone 3 mL/100 mL; octocrylene 2.7 mL/100 mL
INACTIVE INGREDIENTS: water; butylene glycol; isononyl isononanoate; butyloctyl salicylate; triacontanyl pvp (wp-660); silicon dioxide; rosemary; perilla frutescens leaf; caffeine; sucrose; potassium cetyl phosphate; peg-100 stearate; cetyl alcohol; high density polyethylene; .alpha.-tocopherol acetate; tromethamine; magnesium ascorbyl phosphate; hyaluronate sodium; maltodextrin; caprylyl glycol; hexylene glycol; masoprocol; ferulic acid; edetate disodium; phenoxyethanol; chlorphenesin; mica

CLINIQUE
SPF
15
with
SolarSmart

TO USE

Apply liberally before sun exposure and as needed. Children under 6 months of age: ask a doctor. Reapply frequently, and after towel drying, swimming or perspiring.

WARNING

For external use only. Keep out of eyes. Rinse with water to remove.

Stop use and ask a doctor if rash or irritation develops and lasts.

Keep out of reach of children. If swallowed, get medical help right away.

ACTIVE INGREDIENTS

HOMOSALATE 10.0% • OCTISALATE 5.0% • AVOBENZONE 3.0% • OCTOCRYLENE 2.7%

INGREDIENTS

WATER • BUTYLENE GLYCOL • ISONONYL ISONONANDATE • BUTYLOCTYL SALICYLATE • TRIACONTANYL PVP • POLYESTER-8 • SILICA • ROSMARINUS OFFICINALIS (ROSEMARY) EXTRACT • PERILLA OCYMOIDES LEAF EXTRACT • STEARYL DIMETHICONE • CAFFEINE • PLANKTON EXTRACT • SUCROSE • HYDROGENATED LECITHIN • POTASSIUM CETYL PHOSPHATE • LAURDIMONIUM HYDROXYPROPYL HYDROLYZED SOY PROTEIN • PEG-100 STEARATE • CETYL ALCOHOL • POLYETHYLENE • ACRYLIC ACID/VP CROSSPOLYMER • VP/EICOSENE COPOLYMER • TOCOPHERYL ACETATE • TROMETHAMINE • SODIUM RNA • ALOE BARBADENSIS POWDER • PHOSPHOLIPIDS • LECITHIN • MAGNESIUM ASCORBYL PHOSPHATE • SODIUM HYALURONATE • HYDROXYPROPYL METHYLCELLULOSE • C1-8 ALKYL TETRAHYDROXYCYCLOHEXANOATE • HYDROXYETHYLCELLULOSE • ASCORBYL TOCOPHERYL MALEATE • MALTODEXTRIN • CAPRYLYL GLYCOL • HEXYLENE GLYCOL • NORDIHYDROGUAIARETIC ACID • FERULIC ACID • DISODIUM EDTA • PHENOXYETHANOL • CHLORPHENESIN • MICA [ILN34995]

CLINIQUE LABORATORIES, DIST. NEW YORK, N.Y. 10022

PRINCIPAL DISPLAY PANEL - 150 ml Carton

CLINIQUE

SPF
15
with SolarSmart

UVA UVB
advanced
protection

face/body
cream

5 FL. OZ.
150 ml e